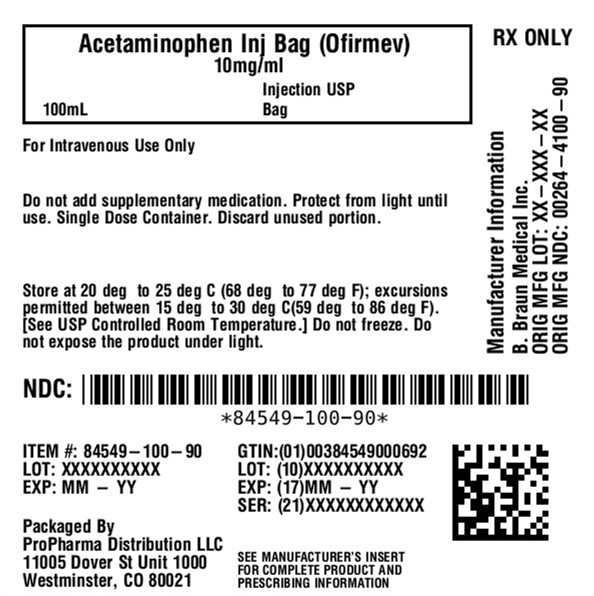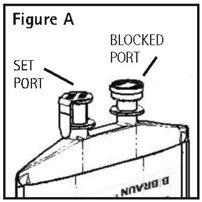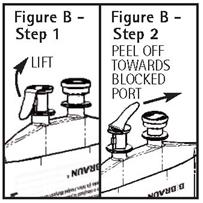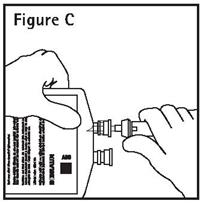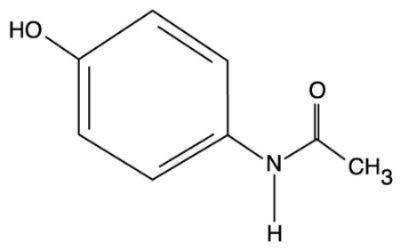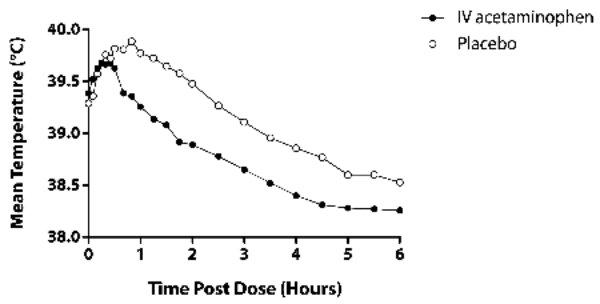 DRUG LABEL: Acetaminophen
NDC: 84549-100 | Form: INJECTION
Manufacturer: ProPharma Distribution
Category: prescription | Type: HUMAN PRESCRIPTION DRUG LABEL
Date: 20250923

ACTIVE INGREDIENTS: ACETAMINOPHEN 10 mg/1 mL
INACTIVE INGREDIENTS: MANNITOL 38 mg/1 mL; SODIUM CITRATE 0.3 mg/1 mL; WATER

HIGHLIGHTS OF PRESCRIBING INFORMATION

These highlights do not include all the information needed to use ACETAMINOPHEN INJECTION safely and effectively. See full prescribing information for ACETAMINOPHEN INJECTION.
ACETAMINOPHEN injection, for intravenous use
Initial U.S. Approval: 1951

WARNING: RISK OF MEDICATION ERRORS AND HEPATOTOXICITY

See full prescribing information for complete boxed warning.

Take care when prescribing, preparing, and administering Acetaminophen Injection to avoid dosing errors which could result in accidental overdose and death. (5.3)

Acetaminophen Injection contains acetaminophen. Acetaminophen has been associated with cases of acute liver failure, at times resulting in liver transplant and death. Most of the cases of liver injury are associated with the use of acetaminophen at doses that exceed the recommended maximum daily limits, and often involve more than one acetaminophen-containing product. (5.1)

1 INDICATIONS AND USAGE

Acetaminophen Injection is indicated for the

- Management of mild to moderate pain in adult and pediatric patients 2 years and older (1)
- Management of moderate to severe pain with adjunctive opioid analgesics in adult and pediatric patients 2 years and older (1)
- Reduction of fever in adult and pediatric patients (1)

2 DOSAGE AND ADMINISTRATION

- Acetaminophen Injection may be given as a single or repeated dose. (2.1)
- Acetaminophen Injection should be administered only as a 15-minute intravenous infusion. (2.5)

Adults and Adolescents Weighing 50 kg and Over:

- 1,000 mg every 6 hours or 650 mg every 4 hours to a maximum of 4,000 mg per day. Minimum dosing interval of 4 hours. (2.2)

Adults and Adolescents Weighing Under 50 kg:

- 15 mg/kg every 6 hours or 12.5 mg/kg every 4 hours to a maximum of 75 mg/kg per day. Minimum dosing interval of 4 hours. (2.2)

Children:

- Children 2 to 12 years of age: 15 mg/kg every 6 hours or 12.5 mg/kg every 4 hours to a maximum of 75 mg/kg per day. Minimum dosing interval of 4 hours. (2.3)

Neonates and Infants:

- Neonates including premature neonates born at greater than or equal to 32 weeks gestational age to 28 days chronological age, 12.5 mg/kg every 6 hours to a maximum of 50 mg/kg per day. Minimum dosing interval of 6 hours. (2.4)
- Infants (29 days to 2 years of age): 15 mg/kg every 6 hours to a maximum of 60 mg/kg per day. Minimum dosing interval of 6 hours. (2.4)

3 DOSAGE FORMS AND STRENGTHS

- 1,000 mg acetaminophen in 100 mL (10 mg/mL) injection for intravenous infusion (3)
- 500 mg acetaminophen in 50 mL (10 mg/mL) injection for intravenous infusion (3)

4 CONTRAINDICATIONS

Acetaminophen is contraindicated:

- In patients with known hypersensitivity to acetaminophen or to any of the excipients in the IV formulation. (4)
- In patients with severe hepatic impairment or severe active liver disease. (4)

5 WARNINGS AND PRECAUTIONS

- Risk of Hepatic Injury: Administration of acetaminophen in doses higher than recommended (by all routes of administration and from all acetaminophen-containing products including combination products) may result in hepatic injury, including the risk of liver failure and death. (5.1)
- Use caution when administering acetaminophen in patients with the following conditions: hepatic impairment or active hepatic disease, in cases of alcoholism, chronic malnutrition, severe hypovolemia, or severe renal impairment (creatinine clearance less than or equal to 30 mL/min). (5.1)
- Risk of Serious Skin or Hypersensitivity Reactions: Discontinue Acetaminophen Injection immediately at the first appearance of skin rash and if symptoms associated with allergy or hypersensitivity occur. Do not use in patients with acetaminophen allergy. (5.2, 5.4)
- Take care when prescribing, preparing, and administering Acetaminophen Injection to avoid dosing errors which could result in accidental overdose and death. (5.3)

6 ADVERSE REACTIONS

The most common adverse reactions (incidence greater than or equal to 5%) in patients treated with Acetaminophen Injection were nausea, vomiting, headache, and insomnia in adult patients; nausea, vomiting, constipation and pruritus in pediatric patients. (6.1)

To report SUSPECTED ADVERSE REACTIONS, contact B. Braun Medical Inc. at 1-800-854-6851or FDA at 1-800-FDA-1088 or www.fda.gov/medwatch.

7 DRUG INTERACTIONS

- Substances that induce or regulate hepatic cytochrome enzyme CYP2E1 may alter the metabolism of acetaminophen and increase its hepatotoxic potential. (7.1)
- Chronic oral acetaminophen use at a dose of 4,000 mg/day has been shown to cause an increase in international normalized ratio (INR) in some patients who have been stabilized on sodium warfarin as an anticoagulant. (7.2)

8 USE IN SPECIFIC POPULATIONS

- Pediatric Use: The effectiveness of acetaminophen for the treatment of acute pain in pediatric patients younger than 2 years of age has not been established. The safety and effectiveness of acetaminophen in pediatric patients is supported by evidence from adequate and well controlled studies in adults with additional safety and pharmacokinetic data for this age group. (8.4)
- Geriatric Use: No overall differences in safety or effectiveness were observed between geriatric and younger subjects. (8.5)
- Hepatic Impairment: Acetaminophen is contraindicated in patients with severe hepatic impairment or severe active liver disease and should be used with caution in patients with hepatic impairment or active liver disease. (4, 5.1, 8.6)
- Renal Impairment: In cases of severe renal impairment, longer dosing intervals and a reduced total daily dose of acetaminophen may be warranted. (5.1, 8.7)

FULL PRESCRIBING INFORMATION

WARNING: RISK OF MEDICATION ERRORS AND HEPATOTOXICITY

Take care when prescribing, preparing, and administering Acetaminophen Injection to avoid dosing errors which could result in accidental overdose and death. In particular, be careful to ensure that:

- the dose in milligrams (mg) and milliliters (mL) is not confused;
- the dosing is based on weight for patients under 50 kg;
- infusion pumps are properly programmed; and
- the total daily dose of acetaminophen from all sources does not exceed maximum daily limits.

Acetaminophen Injection contains acetaminophen. Acetaminophen has been associated with cases of acute liver failure, at times resulting in liver transplant and death. Most of the cases of liver injury are associated with the use of acetaminophen at doses that exceed the maximum daily limits, and often involve more than one acetaminophen-containing product [see Warnings and Precautions (5.1)].

1 INDICATIONS AND USAGE

Acetaminophen Injection is indicated for

- the management of mild to moderate pain in adult and pediatric patients 2 years and older
- the management of moderate to severe pain with adjunctive opioid analgesics in adult and pediatric patients 2 years and older
- the reduction of fever in adult and pediatric patients.

2 DOSAGE AND ADMINISTRATION

2.1 Important Dosing and Administration Information

- DO NOT ADD SUPPLEMENTARY MEDICATION.
- Aseptic technique is required.
- Before use, perform the following checks: Read the label. Ensure solution is the one ordered and is within the expiration date.
- Inspect the solution in good light for cloudiness, haze or particulate matter; check the container for leakage or damage. Any container which is suspect should not be used.
- Use only if solution is clear and container and seals are intact. Single-dose plastic container. Discard unused portion. Consult Package Insert for complete product information.
- DO NOT USE PLASTIC CONTAINER IN SERIES CONNECTION.

Acetaminophen Injection may be given as a single or repeated dose for the treatment of acute pain or fever. No dose adjustment is required when converting between oral acetaminophen and Acetaminophen Injection dosing in adults and adolescents who weigh 50 kg and above. Calculated maximum daily dose of acetaminophen is based on all routes of administration (i.e. intravenous, oral, and rectal) and all products containing acetaminophen. Exceeding the maximum mg/kg daily dose of acetaminophen as described in Tables 1-3 may result in hepatic injury, including the risk of liver failure and death. To avoid the risk of overdose, ensure that the total amount of acetaminophen from all routes and from all sources does not exceed the maximum recommended dose.

2.2 Recommended Dosage: Adults and Adolescents

Adults and adolescents weighing 50 kg and over: the recommended dosage of Acetaminophen Injection is 1,000 mg every 6 hours or 650 mg every 4 hours, with a maximum single dose of Acetaminophen Injection of 1,000 mg, a minimum dosing interval of 4 hours, and a maximum daily dose of acetaminophen of 4,000 mg per day (includes all routes of administration and all acetaminophen-containing products including combination products).

Adults and adolescents weighing under 50 kg: the recommended dosage of Acetaminophen Injection is 15 mg/kg every 6 hours or 12.5 mg/kg every 4 hours, with a maximum single dose of Acetaminophen Injection of 15 mg/kg, a minimum dosing interval of 4 hours, and a maximum daily dose of acetaminophen of 75 mg/kg per day (includes all routes of administration and all acetaminophen-containing products including combination products).

Table 1. Dosing for Adults and Adolescents
Age group | Dose given every 4 hours | Dose given every 6 hours | Maximum single dose | Maximum total daily dose of acetaminophen (by all routes)
Adults and adolescents (13 years and older) weighing greater than or equal to 50 kg | 650 mg | 1,000 mg | 1,000 mg | 4,000 mg in 24 hours
Adults and adolescents (13 years and older) weighing less than 50 kg | 12.5 mg/kg | 15 mg/kg | 15 mg/kg (up to 750 mg) | 75 mg/kg in 24 hours (up to 3,750 mg)

2.3 Recommended Dosage: Children

Children 2 to 12 years of age: the recommended dosage of Acetaminophen Injection is 15 mg/kg every 6 hours or 12.5 mg/kg every 4 hours, with a maximum single dose of Acetaminophen Injection of 15 mg/kg, a minimum dosing interval of 4 hours, and a maximum daily dose of acetaminophen of 75 mg/kg per day.

Table 2. Dosing for Children
Age group | Dose given every 4 hours | Dose given every 6 hours | Maximum single dose | Maximum total daily dose of acetaminophen (by all routes)
Children 2 to 12 years of age | 12.5 mg/kg | 15 mg/kg | 15 mg/kg (up to 750 mg) | 75 mg/kg in 24 hours (up to 3,750 mg)

2.4 Recommended Dosage for Treatment of Fever in Neonates and Infants

Neonates, including premature neonates born at greater than or equal to 32 weeks gestational age, up to 28 days chronological age: the recommended dosage of Acetaminophen Injection is 12.5 mg/kg every 6 hours, to a maximum daily dose of acetaminophen of 50 mg/kg per day, with a minimum dosing interval of 6 hours.

Infants 29 days to 2 years of age: the recommended dosage of Acetaminophen Injection is 15 mg/kg every 6 hours, to a maximum daily dose of acetaminophen of 60 mg/kg per day, with a minimum dosing interval of 6 hours.

Table 3. Dosing for Treatment of Fever in Neonates and Infants
Age group | Dose given every 6 hours | Maximum total daily dose of acetaminophen (by all routes)
Neonates (birth to 28 days) | 12.5 mg/kg | 50 mg/kg
Infants (29 days to 2 years) | 15 mg/kg | 60 mg/kg

2.5 Instructions for Intravenous Administration from PAB® Container

DO NOT ADD SUPPLEMENTARY MEDICATION.

Aseptic technique is required.

Before use, perform the following checks: Read the label. Ensure solution is the one ordered and is within the expiration date.

Inspect the solution in good light for cloudiness, haze or particulate matter; check the container for leakage or damage. Any container which is suspect should not be used.

Use only if solution is clear and container and seals are intact. Single dose plastic container. Discard unused portion. Consult Package Insert for complete product information.

DO NOT USE PLASTIC CONTAINER IN SERIES CONNECTION.

This solution is intended for intravenous administration over 15 minutes using sterile equipment. It is recommended that intravenous administration apparatus be replaced at least once every 24 hours.

1. Identify Two Ports (See Figure A).

2. To Attach Administration Set

To aseptically remove the set port closure: hold container below the set port and grasp the foil tab between the thumb and forefinger then pull the tab in two steps as shown in Figure B Steps 1 and 2.

3. Push spike through the diaphragm of the port (See Figure C). Hang container using hole on the lower flap. Prime set in accordance with the Directions for Useprovided with the set in use.

PAB® containers can be safely transported in a standard 6-inch carrier through a pneumatic tube system that is well maintained and running properly.

2.6 Instructions for Intravenous Administration of Doses Not Equivalent to 500 mg or 1,000 mg

Doses that are not equivalent to 500 mg or 1,000 mg require aseptic transfer to a separate container prior to dispensing. Discard unused portion. Using aseptic technique, withdraw the appropriate dose (650 mg or weight-based) from an intact sealed PAB container and place the measured dose in a separate empty, sterile container (e.g., glass bottle, plastic intravenous container, or syringe) for intravenous infusion to avoid the inadvertent delivery and administration of the total volume of the commercially available container. The entire 100 mL container is not intended for use in patients weighing less than 50 kg. Acetaminophen injection is supplied in a single-dose container and the unused portion must be discarded.

Place small volume pediatric doses up to 60 mL in volume in a syringe and administer over 15 minutes using a syringe pump.

3 DOSAGE FORMS AND STRENGTHS

Acetaminophen Injection is a sterile, clear, colorless, non-pyrogenic, preservative free, isotonic formulation of acetaminophen available as:

- 1,000 mg acetaminophen in 100 mL (10 mg/mL) injection for intravenous infusion
- 500 mg acetaminophen in 50 mL (10 mg/mL) injection for intravenous infusion

4 CONTRAINDICATIONS

Acetaminophen is contraindicated:

- in patients with known hypersensitivity to acetaminophen or to any of the excipients in the intravenous formulation.
- in patients with severe hepatic impairment or severe active liver disease [see Warnings and Precautions (5.1)].

5 WARNINGS AND PRECAUTIONS

5.1 Hepatic Injury

Administration of acetaminophen in doses higher than recommended may result in hepatic injury, including the risk of liver failure and death [see Overdosage (10)]. Do not exceed the maximum recommended daily dose of acetaminophen [see Dosage and Administration (2)]. The maximum recommended daily dose of acetaminophen includes all routes of acetaminophen administration and all acetaminophen-containing products administered, including combination products.

Use caution when administering acetaminophen in patients with the following conditions: hepatic impairment or active hepatic disease, alcoholism, chronic malnutrition, severe hypovolemia (e.g., due to dehydration or blood loss), or severe renal impairment (creatinine clearance less than or equal to 30 mL/min) [see Use In Specific Populations (8.6, 8.7)].

5.2 Serious Skin Reactions

Rarely, acetaminophen may cause serious skin reactions such as acute generalized exanthematous pustulosis (AGEP), Stevens-Johnson Syndrome (SJS), and toxic epidermal necrolysis (TEN), which can be fatal. Patients should be informed about the signs of serious skin reactions, and use of the drug should be discontinued at the first appearance of skin rash or any other sign of hypersensitivity.

5.3 Risk of Medication Errors

Take care when prescribing, preparing, and administering Acetaminophen Injection in order to avoid dosing errors which could result in accidental overdose and death. In particular, be careful to ensure that:

- the dose in milligrams (mg) and milliliters (mL) is not confused;
- the dosing is based on weight for patients under 50 kg;
- infusion pumps are properly programmed; and
- the total daily dose of acetaminophen from all sources does not exceed maximum daily limits [see Dosage and Administration (2) ].

5.4 Allergy and Hypersensitivity

There have been post-marketing reports of hypersensitivity and anaphylaxis associated with the use of acetaminophen. Clinical signs included swelling of the face, mouth, and throat, respiratory distress, urticaria, rash, and pruritus. There were infrequent reports of life-threatening anaphylaxis requiring emergent medical attention. Discontinue Acetaminophen Injection immediately if symptoms associated with allergy or hypersensitivity occur. Do not use Acetaminophen Injection in patients with acetaminophen allergy.

6 ADVERSE REACTIONS

The following serious adverse reactions are discussed elsewhere in the labeling:

- Hepatic Injury [see Warnings and Precautions (5.1)]
- Serious Skin Reactions [see Warnings and Precautions (5.2)]
- Allergy and Hypersensitivity [see Warnings and Precautions (5.4)]

6.1 Clinical Trial Experience

Because clinical trials are conducted under widely varying conditions, adverse reaction rates observed cannot be directly compared to rates in other clinical trials and may not reflect the rates observed in practice.

Adult Population

A total of 1,020 adult patients have received Acetaminophen Injection in clinical trials, including 37.3% (n=380) who received 5 or more doses, and 17.0% (n=173) who received more than 10 doses. Most patients were treated with Acetaminophen Injection 1,000 mg every 6 hours. A total of 13.1% (n=134) received Acetaminophen Injection 650 mg every 4 hours.

All adverse reactions that occurred in adult patients treated with either Acetaminophen Injection or placebo in repeated dose, placebo-controlled clinical trials at an incidence greater than or equal to 3% and at a greater frequency than placebo are listed in Table 4. The most common adverse events in adult patients treated with Acetaminophen Injection (incidence greater than or equal to 5% and greater than placebo) were nausea, vomiting, headache, and insomnia.

Table 4. Treatment-Emergent Adverse Reactions Occurring in greater than or equal to 3% of Acetaminophen Injection-treated Adult Patients and at a Greater Frequency than Placebo in Placebo-Controlled, Repeated Dose Studies
System Organ Class – Preferred Term | Acetaminophen Injection (N=402) n (%) | Placebo (N=379) n (%)
Gastrointestinal Disorders Nausea Vomiting | 138 (34) 62 (15) | 119 (31) 42 (11)
General Disorders and Administration Site Conditions Pyrexia* | 22 (5) | 52 (14)
Nervous System Disorders Headache | 39 (10) | 33 (9)
Psychiatric Disorders Insomnia | 30 (7) | 21 (5)
* Pyrexia adverse reaction frequency data is included in order to alert healthcare practitioners that the antipyretic effects of Acetaminophen Injection may mask fever.

Other Adverse Reactions Observed During Clinical Studies of Acetaminophen Injection in Adults

The following additional treatment-emergent adverse reactions were reported by adult subjects treated with Acetaminophen Injection in all clinical trials (n=1,020) that occurred with an incidence of at least 1% and at a frequency greater than placebo (n=525).

Blood and lymphatic system disorders:anemia

General disorders and administration site conditions:fatigue, infusion site pain, edema peripheral

Investigations:aspartate aminotransferase increased, breath sounds abnormal

Metabolism and nutrition disorders:hypokalemia

Musculoskeletal and connective tissue disorders:muscle spasms, trismus

Psychiatric disorders:anxiety

Respiratory, thoracic and mediastinal disorders:dyspnea

Vascular disorders:hypertension, hypotension

Pediatric Population

A total of 483 pediatric patients (72 neonates, 167 infants, 171 children, and 73 adolescents) have received Acetaminophen Injection in active-controlled (n=250) and open-label clinical trials (n=225), including 43.9% (n=212) who received 5 or more doses and 31.2% (n=153) who received more than 10 doses. Pediatric patients received Acetaminophen Injection doses up to 15 mg/kg on an every 4 hours, every 6 hours, or every 8 hours schedule. The maximum exposure was 7.7, 6.4, 6.8, and 7.1 days in neonates, infants, children, and adolescents, respectively.

The most common adverse events (incidence greater than or equal to 5%) in pediatric patients treated with Acetaminophen Injection were nausea, vomiting, constipation, and pruritus.

Other Adverse Reactions Observed During Clinical Studies of Acetaminophen Injection in Pediatrics

The following additional treatment-emergent adverse reactions were reported by pediatric subjects treated with Acetaminophen Injection (n=483) that occurred with an incidence of at least 1%.

Blood and lymphatic system disorders:anemia

Gastrointestinal disorders:diarrhea

General disorders and administration site conditions: pyrexia, injection site pain

Metabolism and nutrition disorders:hypokalemia, hypomagnesemia, hypoalbuminemia, hypophosphatemia

Musculoskeletal and connective tissue disorders:muscle spasm

Nervous system disorders:headache

Psychiatric disorders:agitation

Renal and urinary disorders:oliguria

Respiratory, thoracic and mediastinal disorders:atelectasis, pleural effusion, pulmonary edema, stridor, wheezing

Vascular disorders:hypotension, hypertension

7 DRUG INTERACTIONS

7.1 Effects of Other Substances on Acetaminophen

Substances that induce or regulate hepatic cytochrome enzyme CYP2E1 may alter the metabolism of acetaminophen and increase its hepatotoxic potential. The clinical consequences of these effects have not been established. Effects of ethanol are complex, because excessive alcohol usage can induce hepatic cytochromes, but ethanol also acts as a competitive inhibitor of the metabolism of acetaminophen.

7.2 Anticoagulants

Chronic oral acetaminophen use at a dose of 4,000 mg/day has been shown to cause an increase in international normalized ratio (INR) in some patients who have been stabilized on sodium warfarin as an anticoagulant. As no studies have been performed evaluating the short-term use of Acetaminophen Injection in patients on oral anticoagulants, more frequent assessment of INR may be appropriate in such circumstances.

8 USE IN SPECIFIC POPULATIONS

8.1 Pregnancy

Risk Summary

Published epidemiological studies with oral acetaminophen use during pregnancy have not reported a definitive association with acetaminophen use and birth defects, miscarriage, or adverse maternal or fetal outcomes [see Data] . Animal reproduction studies have not been conducted with IV acetaminophen. Reproductive and developmental studies in rats and mice from the published literature identified adverse events at clinically relevant doses with acetaminophen. Treatment of pregnant rats with doses of acetaminophen approximately equal to the maximum human daily dose (MHDD) showed evidence of fetotoxicity and increases in bone variations in the fetuses. In another study, necrosis was observed in the liver and kidney of both pregnant rats and fetuses at doses approximately equal to the MHDD. In mice and rats treated with acetaminophen at doses within the clinical dosing range, cumulative adverse effects on reproductive capacity were reported. In mice, a reduction in number of litters of the parental mating pair was observed as well as retarded growth, abnormal sperm in their offspring and reduced birth weight in the next generation. In rats, female fertility was decreased following in utero exposure to acetaminophen [see Data] .

The estimated background risk of major birth defects and miscarriages for the indicated population is unknown. All pregnancies have a background risk of birth defect, loss, or other adverse outcomes. In the U.S. general population, the estimated background risk of major birth defects and miscarriage in clinically recognized pregnancies is 2-4% and 15-20%, respectively.

Data

Human Data

The results from a large population-based prospective cohort, including data from 26,424 women with live born singletons who were exposed to oral acetaminophen during the first trimester, indicate no increased risk for congenital malformations, compared to a control group of unexposed children. The rate of congenital malformations (4.3%) was similar to the rate in the general population. A population-based, case-control study from the National Birth Defects Prevention Study showed that 11,610 children with prenatal exposure to acetaminophen during the first trimester had no increased risk of major birth defects compared to 4,500 children in the control group. Other epidemiological data showed similar results. However, these studies cannot definitely establish the absence of any risk because of methodological limitations, including recall bias.

Animal Data

Studies in pregnant rats that received oral acetaminophen during organogenesis at doses up to 0.85 times the maximum human daily dose (MHDD = 4 grams/day, based on a body surface area comparison) showed evidence of fetotoxicity (reduced fetal weight and length) and a dose-related increase in bone variations (reduced ossification and rudimentary rib changes). Offspring had no evidence of external, visceral, or skeletal malformations. When pregnant rats received oral acetaminophen throughout gestation at doses of 1.2 times the MHDD (based on a body surface area comparison), areas of necrosis occurred in both the liver and kidney of pregnant rats and fetuses. These effects did not occur in animals that received oral acetaminophen at doses 0.3 times the MHDD, based on a body surface area comparison.

In a continuous breeding study, pregnant mice received 0.25, 0.5, or 1.0% acetaminophen via the diet (357, 715, or 1,430 mg/kg/day). These doses are approximately 0.43, 0.87, and 1.7 times the MHDD, respectively, based on a body surface area comparison. A dose related reduction in body weights of fourth and fifth litter offspring of the treated mating pair occurred during lactation and post-weaning at all doses. Animals in the high dose group had a reduced number of litters per mating pair, male offspring with an increased percentage of abnormal sperm, and reduced birth weights in the next generation pups.

8.2 Lactation

Risk Summary

There is no information regarding the presence of Acetaminophen Injection in human milk, the effects on the breastfed infant, or the effects on milk production. However, limited published studies report that acetaminophen passes rapidly into human milk with similar levels in the milk and plasma. Average and maximum, neonatal doses of 1% and 2%, respectively, of the weight-adjusted maternal dose are reported after a single oral administration of 1 gram APAP. There is one well-documented report of a rash in a breast-fed infant that resolved when the mother stopped acetaminophen use and recurred when she resumed acetaminophen use. The developmental and health benefits of breastfeeding should be considered along with the mother’s clinical need for Acetaminophen Injection and any potential adverse effects on the breastfed infant from Acetaminophen Injection or from the underlying maternal condition.

8.3 Females and Males of Reproductive Potential

Based on animal data use of acetaminophen may cause reduced fertility in males and females of reproductive potential. It is not known whether these effects on fertility are reversible. Published animal studies reported that oral acetaminophen treatment of male animals at doses that are 1.2 times the MHDD and greater (based on a body surface area comparison) result in decreased testicular weights, reduced spermatogenesis, and reduced fertility. In female animals given the same doses, reduced implantation sites were reported. Additional published animal studies indicate that acetaminophen exposure in utero adversely impacts reproductive capacity of both male and female offspring at clinically relevant exposures [see Nonclinical Toxicology (13.1)].

8.4 Pediatric Use

Treatment of Acute Pain

The safety and effectiveness of Acetaminophen Injection for the treatment of acute pain in pediatric patients ages 2 years and older is supported by evidence from adequate and well-controlled studies of Acetaminophen Injection in adults and safety and pharmacokinetic data from adult and 483 pediatric patients across all age groups [see Dosage and Administration (2.3)and Pharmacokinetics (12.3)].

The effectiveness of Acetaminophen Injection for the treatment of acute pain in pediatric patients younger than 2 years of age has not been established.

In patients younger than 2 years, efficacy was not demonstrated in a double-blind, placebo-controlled study of 198 pediatric patients younger than 2 years. Pediatric patients less than 2 years of age, including neonates from 28 to 40 weeks gestational age at birth, were randomized to receive opioid plus acetaminophen or opioid plus placebo. No difference in analgesic effect of intravenous acetaminophen, measured by assessment of reduced need for additional opioid treatment for pain control, was observed.

Treatment of Fever

The safety and effectiveness of Acetaminophen Injection for the treatment of fever in pediatric patients, including premature neonates born at greater than or equal to 32 weeks gestational age is supported by adequate and well-controlled studies of Acetaminophen Injection in adults, clinical studies in 244 pediatric patients 2 years and older, and safety and pharmacokinetic data from 239 patients younger than 2 years including neonates greater than or equal to 32 weeks gestational age.

8.5 Geriatric Use

Of the total number of subjects in clinical studies of acetaminophen, 15% were age 65 and over, while 5% were age 75 and over. No overall differences in safety or effectiveness were observed between these subjects and younger subjects, and other reported clinical experience has not identified differences in responses between the elderly and younger patients, but greater sensitivity of some older individuals cannot be ruled out.

8.6 Patients with Hepatic Impairment

Acetaminophen is contraindicated in patients with severe hepatic impairment or severe active liver disease and should be used with caution in patients with hepatic impairment or active liver disease [see Warnings and Precautions (5.1)and Clinical Pharmacology (12)]. A reduced total daily dose of acetaminophen may be warranted.

8.7 Patients with Renal Impairment

In cases of severe renal impairment (creatinine clearance less than or equal to 30 mL/min), longer dosing intervals and a reduced total daily dose of acetaminophen may be warranted.

10 OVERDOSAGE

Clinical Presentation

In acute acetaminophen overdosage, dose-dependent, potentially fatal hepatic necrosis is the most serious adverse effect. Renal tubular necrosis, hypoglycemic coma, and thrombocytopenia may also occur. Plasma acetaminophen levels greater than 300 mcg/mL at 4 hours after oral ingestion were associated with hepatic damage in 90% of patients; minimal hepatic damage is anticipated if plasma levels at 4 hours are less than 150 mcg/mL or less than 37.5 mcg/mL at 12 hours after ingestion. Early symptoms following a potentially hepatotoxic overdose may include: nausea, vomiting, diaphoresis, and general malaise. Clinical and laboratory evidence of hepatic toxicity may not be apparent until 48 to 72 hours post-ingestion.

Treatment of Overdose

If an acetaminophen overdose is suspected, obtain a serum acetaminophen assay as soon as possible, but no sooner than 4 hours following oral ingestion. Obtain liver function studies initially and repeat at 24-hour intervals. Administer the antidote N-acetylcysteine (NAC) as early as possible. As a guide to treatment of acute ingestion, the acetaminophen level can be plotted against time since oral ingestion on a nomogram (Rumack-Matthew). The lower toxic line on the nomogram is equivalent to 150 mcg/mL at 4 hours and 37.5 mcg/mL at 12 hours. If serum level is above the lower line, administer the entire course of NAC treatment. Withhold NAC therapy if the acetaminophen level is below the lower line.

For additional information, call a poison control center at 1-800-222-1222.

11 DESCRIPTION

Acetaminophen is a non-salicylate antipyretic and non-opioid analgesic agent. Its chemical name is N-acetyl-p-aminophenol.

Acetaminophen has a molecular weight of 151.16. Its structural formula is:

Acetaminophen Injection is a sterile, clear, colorless, non pyrogenic, isotonic formulation of acetaminophen intended for intravenous infusion. It has a pH of approximately 5.0 and an osmolality of approximately 290 mOsm/kg.

Each 100 mL contains 1,000 mg Acetaminophen, USP, 3,800 mg Mannitol, USP, 30 mg Sodium Citrate Dihydrate USP, and Water for Injection, USP qs.

Each 50 mL contains 500 mg Acetaminophen, USP, 1,900 mg Mannitol, USP, 15 mg Sodium Citrate Dihydrate USP, and Water for Injection, USP qs.

pH is adjusted with glacial acetic acid.

Not made with natural rubber latex, PVC or DEHP.

12 CLINICAL PHARMACOLOGY

12.1 Mechanism of Action

The precise mechanism of the analgesic and antipyretic properties of acetaminophen is not established but is thought to primarily involve central actions.

12.2 Pharmacodynamics

Acetaminophen has been shown to have analgesic and antipyretic activities in animal and human studies. Single doses of acetaminophen up to 3,000 mg and repeated doses of 1,000 mg every 6 hours for 48 hours have not been shown to cause a significant effect on platelet aggregation. Acetaminophen does not have any immediate or delayed effects on small-vessel hemostasis. Clinical studies of both healthy subjects and patients with hemophilia showed no significant changes in bleeding time after receiving multiple doses of oral acetaminophen.

12.3 Pharmacokinetics

Distribution

The pharmacokinetics of Acetaminophen Injection have been studied in patients and healthy subjects up to 60 years old. The pharmacokinetic profile of Acetaminophen Injection has been demonstrated to be dose proportional in adults following administration of single doses of 500, 650, and 1,000 mg.

The maximum concentration (Cmax) occurs at the end of the 15-minute intravenous infusion of Acetaminophen Injection. Compared to the same dose of oral acetaminophen, the Cmaxfollowing administration of Acetaminophen Injection is up to 70% higher, while overall exposure (area under the concentration time curve [AUC]) is very similar.

Pharmacokinetic parameters of Acetaminophen Injection (AUC, Cmax, terminal elimination half-life [T½], systemic clearance [CL], and volume of distribution at steady state [Vss]) following administration of a single intravenous dose of 15 mg/kg in children and adolescents and 1,000 mg in adults are summarized in Table 5.

Table 5. Acetaminophen Injection Pharmacokinetic Parameters
Subpopulations | Mean (SD)
Subpopulations | AUC0-6h (mcg × h/mL) | Cmax (mcg/mL) | T½ (h) | CL (L/h/kg) | Vss (L/kg)
Children | 38 (8) | 29 (7) | 3.0 (1.5) | 0.34 (0.10) | 1.2 (0.3)
Adolescents | 41 (7) | 31 (9) | 2.9 (0.7) | 0.29 (0.08) | 1.1 (0.3)
Adults | 43 (11) | 28 (21) | 2.4 (0.6) | 0.27 (0.08) | 0.8 (0.2)

The concentrations of acetaminophen observed in neonates greater than 32 weeks gestational age at birth treated with 12.5 mg/kg dose are similar to infants, children and adolescents treated with a 15 mg/kg dose, and similar to adults treated with a 1,000 mg dose.

At therapeutic levels, binding of acetaminophen to plasma proteins is low (ranging from 10% to 25%). Acetaminophen appears to be widely distributed throughout most body tissues except fat.

Elimination

Metabolism

Acetaminophen is primarily metabolized in the liver by first-order kinetics and involves three principal separate pathways: Conjugation with glucuronide, conjugation with sulfate, and oxidation via the cytochrome P450 enzyme pathway, primarily CYP2E1, to form a reactive intermediate metabolite (N-acetyl-p-benzoquinone imine or NAPQI). With therapeutic doses, NAPQI undergoes rapid conjugation with glutathione and is then further metabolized to form cysteine and mercapturic acid conjugates.

Excretion

Acetaminophen metabolites are mainly excreted in the urine. Less than 5% is excreted in the urine as unconjugated (free) acetaminophen and more than 90% of the administered dose is excreted within 24 hours.

13 NONCLINICAL TOXICOLOGY

13.1 Carcinogenesis, Mutagenesis, Impairment of Fertility

Carcinogenesis

Long-term studies in mice and rats have been completed by the National Toxicology Program to evaluate the carcinogenic potential of acetaminophen. In 2-year feeding studies, F344/N rats and B6C3F1 mice were fed a diet containing acetaminophen up to 6,000 ppm. Female rats demonstrated equivocal evidence of carcinogenic activity based on increased incidences of mononuclear cell leukemia at 0.8 times the maximum human daily dose (MHDD) of 4 grams/day, based on a body surface area comparison. In contrast, there was no evidence of carcinogenic activity in male rats (0.7 times) or mice (1.2-1.4 times the MHDD, based on a body surface area comparison).

Mutagenesis

Acetaminophen was not mutagenic in the bacterial reverse mutation assay (Ames test). In contrast, acetaminophen tested positive in the in vitromouse lymphoma assay and the in vitrochromosomal aberration assay using human lymphocytes. In the published literature, acetaminophen has been reported to be clastogenic when administered a dose of 1,500 mg/kg/day to the rat model (3.6 times the MHDD, based on a body surface area comparison). In contrast, no clastogenicity was noted at a dose of 750 mg/kg/day (1.8 times the MHDD, based on a body surface area comparison), suggesting a threshold effect.

Impairment of Fertility

In studies conducted by the National Toxicology Program, fertility assessments have been completed in Swiss mice via a continuous breeding study. There were no effects on fertility parameters in mice consuming up to 1.7 times the MHDD of acetaminophen, based on a body surface area comparison. Although there was no effect on sperm motility or sperm density in the epididymis, there was a significant increase in the percentage of abnormal sperm in mice consuming 1.7 times the MHDD (based on a body surface area comparison) and there was a reduction in the number of mating pairs producing a fifth litter at this dose, suggesting the potential for cumulative toxicity with chronic administration of acetaminophen near the upper limit of daily dosing.

Published studies in rodents report that oral acetaminophen treatment of male animals at doses that are 1.2 times the MHDD and greater (based on a body surface area comparison) result in decreased testicular weights, reduced spermatogenesis, reduced fertility, and reduced implantation sites in females given the same doses. These effects appear to increase with the duration of treatment.

In a published mouse study, oral administration of 50 mg/kg acetaminophen to pregnant mice from Gestation Day 7 to delivery (0.06 times the MHDD, based on a body surface area comparison) reduced the number of primordial follicles in female offspring and reduced the percentage of full term pregnancies and number of pups born to these females exposed to acetaminophen in utero.

In published study, oral administration of 350 mg/kg acetaminophen to pregnant rats (0.85 times the MHDD, based on a body surface area comparison) from Gestation Day 13 to 21 (dams) reduced the number of germ cells in the fetal ovary, decreased ovary weight, and reduced the number of pups per litter in F1females as well reduced ovary weights in F2females.

14 CLINICAL STUDIES

14.1 Adult Acute Pain

The efficacy of Acetaminophen Injection in the treatment of acute pain in adults was evaluated in two randomized, double-blind, placebo-controlled clinical trials in patients with postoperative pain.

Pain Study 1evaluated the analgesic efficacy of repeated doses of acetaminophen 1,000 mg vs. placebo every 6 hours for 24 hours in 101 patients with moderate to severe pain following total hip or knee replacement. Acetaminophen Injection was statistically superior to placebo for reduction in pain intensity over 24 hours. There was an attendant decrease in opioid consumption, the clinical benefit of which was not demonstrated.

Pain Study 2evaluated the analgesic efficacy of repeated doses of acetaminophen 1,000 mg every 6 hours or 650 mg every 4 hours for 24 hours versus placebo in the treatment of 244 patients with moderate to severe postoperative pain after abdominal laparoscopic surgery. Patients receiving acetaminophen experienced a statistically significant greater reduction in pain intensity over 24 hours compared to placebo.

14.2 Adult Fever

The efficacy of acetaminophen 1,000 mg in the treatment of adult fever was evaluated in one randomized, double-blind, placebo-controlled clinical trial. The study was a 6-hour, single-dose, endotoxin-induced fever study in 60 healthy adult males. A statistically significant antipyretic effect of acetaminophen was demonstrated through 6 hours in comparison to placebo. The mean temperature over time is shown in Figure 1.

Figure 1: Mean Temperature (°C) Over Time

14.3 Pediatric Acute Pain and Fever

Acetaminophen was studied in pediatric patients in three active-controlled trials and three open-label safety and pharmacokinetic trials [see Use in Specific Populations (8.4)].

16 HOW SUPPLIED/STORAGE AND HANDLING

Acetaminophen Injection (10 mg/mL) is a clear, colorless solution and is supplied sterile and nonpyrogenic in 100 mL fill PAB® container:

NDC |  | Strength
84549-100-90 |  | 1,000 mg/100 mL

Acetaminophen Injection should be stored at 20°C to 25°C (68°F to 77°F); excursions permitted between 15°C to 30°C (59°F to 86°F). [See USP Controlled Room Temperature.] For single dose only. Use the product within 18 hours after opening. Do not freeze.

Protect from light until use.

Use only if prepared solution is clear and free from particulate matter.

PAB is a registered trademark of B. Braun Medical Inc.

Prepared in USA. API from USA or China.